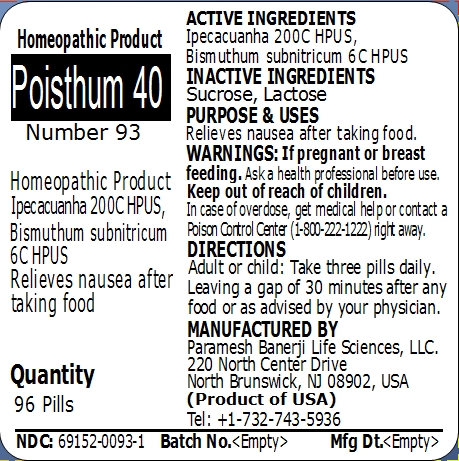 DRUG LABEL: Poisthum 40 (Number 93)
NDC: 69152-0093 | Form: PELLET
Manufacturer: Paramesh Banerji Life Sciences LLC
Category: homeopathic | Type: HUMAN OTC DRUG LABEL
Date: 20150210

ACTIVE INGREDIENTS: IPECAC 200 [hp_C]/1 1; BISMUTH SUBNITRATE 6 [hp_C]/1 1
INACTIVE INGREDIENTS: SUCROSE; LACTOSE

Active Ingredients

Ipecacuanha 200C HPUS, Bismuthum subnitricum 6C HPUS

Inactive Ingredients

Sucrose, Lactose

Purpose

Relieves nausea after taking food

Uses

Relieves nausea after taking food

Warnings

If pregnant or breast feeding ask a health professional before use.

Keep out of reach of children. In case of overdose, get medical help or contact a Poison Control Center (1-800-222-1222) right away.

Direction

Adult or child: Take three pills daily. Leaving a gap of 30 minutes after any food or as advised by your physician.

Manufactured by

Paramesh Banerji Life Sciences, LLC

220 North Center Drive

North Brunswick, NJ 08902, USA

Product of USA

Tel: +1-732-743-5936

Principal Display Panel

Homeopathic Product

Poisthum 40

Number 93

Homeopathic Product

Ipecacuanha 200C HPUS, Bismuthum subnitricum 6C HPUS

Relieves nausea after taking food

Quantity

96 Pills